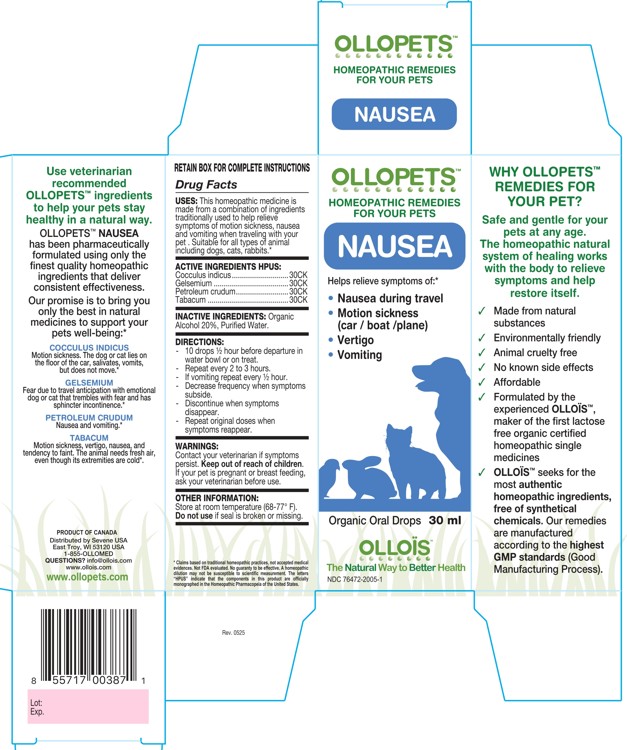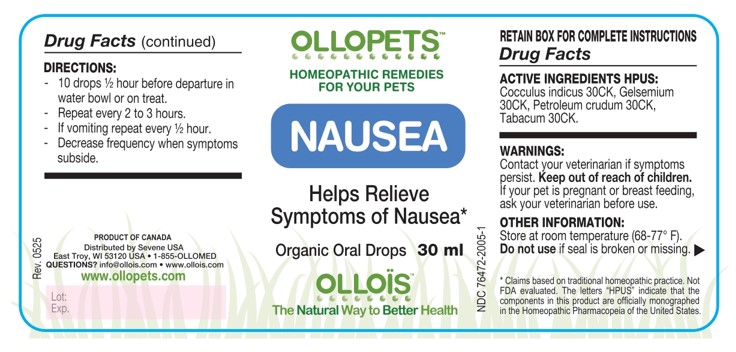 DRUG LABEL: OLLOPETS NAUSEA
NDC: 76472-2005 | Form: SOLUTION
Manufacturer: SEVENE USA
Category: homeopathic | Type: OTC ANIMAL DRUG LABEL
Date: 20260218

ACTIVE INGREDIENTS: ANAMIRTA COCCULUS SEED 30 [hp_C]/100 mL; GELSEMIUM SEMPERVIRENS ROOT 30 [hp_C]/100 mL; KEROSENE 30 [hp_C]/100 mL; TOBACCO LEAF 30 [hp_C]/100 mL
INACTIVE INGREDIENTS: ALCOHOL; WATER

SEVENE USA - OLLOPETS - NAUSEA

ACTIVE INGREDIENT HPUS

Cocculus indicus............................30CK
Gelsemium .....................................30CK
Petroleum crudum..........................30CK
Tabacum ........................................30CK